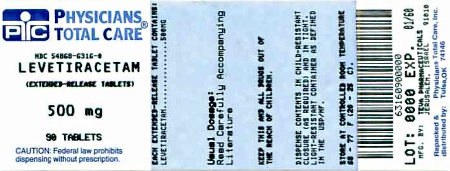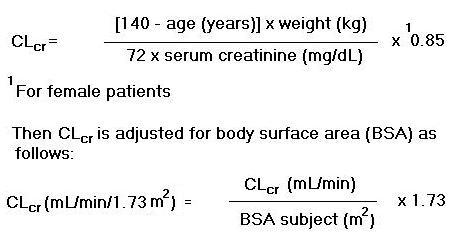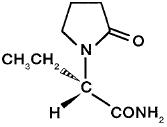 DRUG LABEL: Levetiracetam
NDC: 54868-6316 | Form: TABLET, FILM COATED, EXTENDED RELEASE
Manufacturer: Physicians Total Care, Inc.
Category: prescription | Type: HUMAN PRESCRIPTION DRUG LABEL
Date: 20111213

ACTIVE INGREDIENTS: LEVETIRACETAM 500 mg/1 1
INACTIVE INGREDIENTS: DIBUTYL SEBACATE; ETHYLCELLULOSE (7 MPA.S); HYDROGENATED CASTOR OIL; HYPROMELLOSE 2910 (6 MPA.S); MAGNESIUM STEARATE; CELLULOSE, MICROCRYSTALLINE; POLYETHYLENE GLYCOL 3350; POVIDONE K30; POVIDONE K90; TITANIUM DIOXIDE; FERROSOFERRIC OXIDE; SHELLAC

HIGHLIGHTS OF PRESCRIBING INFORMATION

These highlights do not include all the information needed to use levetiracetam extended-release tablets safely and effectively. See full prescribing information for levetiracetam extended-release tablets.
LEVETIRACETAM extended-release tablets for oral use
Initial U.S. Approval: 1999

RECENT MAJOR CHANGES

Warnings and Precautions (5.1) [04/2009]

Patient Counseling Information (17) [04/2009]

1 INDICATIONS AND USAGE

Levetiracetam extended-release tablets are an antiepileptic drug indicated for adjunctive therapy in the treatment of partial onset seizures in patients ≥ 16 years of age with epilepsy (1)

2 DOSAGE AND ADMINISTRATION

Treatment should be initiated with a dose of 1000 mg once daily. The daily dosage may be adjusted in increments of 1000 mg every 2 weeks to a maximum recommended daily dose of 3000 mg (2).

See full prescribing information for use in patients with impaired renal function (2.1).

3 DOSAGE FORMS AND STRENGTHS

- 500 mg white, film-coated extended-release tablet (3)
- 750 mg white, film-coated extended-release tablet (3)

4 CONTRAINDICATIONS

- None (4)

5 WARNINGS AND PRECAUTIONS

- Suicidal Behavior and Ideation (5.1)
- Neuropsychiatric Adverse Reactions: Levetiracetam extended-release tablets cause somnolence, dizziness, and behavioral abnormalities. The adverse reactions that may be seen in patients receiving levetiracetam extended-release tablets are expected to be similar to those seen in patients receiving immediate-release levetiracetam tablets. (5.2)
- In controlled trials of immediate-release levetiracetam tablets in patients experiencing partial onset seizures, immediate-release levetiracetam causes somnolence and fatigue, coordination difficulties, and behavioral abnormalities (e.g., psychotic symptoms, suicidal ideation, and other abnormalities). (5.2)
- Withdrawal Seizures: Levetiracetam extended-release tablets must be gradually withdrawn. (5.3)

6 ADVERSE REACTIONS

- Most common adverse reactions (difference in incidence rate is ≥ 5% between levetiracetam extended-release tablet-treated patients and placebo-treated patients and occurred more frequently in levetiracetam extended-release tablet-treated patients) include: somnolence and irritability (6.1).
  To report SUSPECTED ADVERSE REACTIONS, contact TEVA USA, PHARMACOVIGILANCE at 1-888-838-2872, X6351 or drug.safety@tevausa.com; or FDA at 1-800-FDA-1088 or www.fda.gov/medwatch.

8 USE IN SPECIFIC POPULATIONS

- To enroll in the North American Antiepileptic Drug Pregnancy Registry call (888) 233-2334 (toll free). (8.1)
- A dose adjustment is recommended for patients with impaired renal function, based on the patient’s estimated creatinine clearance (8.6).

FULL PRESCRIBING INFORMATION

1 INDICATIONS AND USAGE

Levetiracetam extended-release tablets are indicated as adjunctive therapy in the treatment of partial onset seizures in patients ≥ 16 years of age with epilepsy.

2 DOSAGE AND ADMINISTRATION

Treatment should be initiated with a dose of 1000 mg once daily. The daily dosage may be adjusted in increments of 1000 mg every 2 weeks to a maximum recommended daily dose of 3000 mg.

2.1 Adult Patients With Impaired Renal Function

Levetiracetam extended-release tablet dosing must be individualized according to the patient's renal function status. Recommended doses and adjustment for dose for adults are shown in Table 1. To use this dosing table, an estimate of the patient's creatinine clearance (CLcr) in mL/min is needed. CLcr in mL/min may be estimated from serum creatinine (mg/dL) determination using the following formula:

Table 1: Dosing Adjustment Regimen For Adult Patients With Impaired Renal Function
Group | Creatinine Clearance (mL/min/1.73 m^2) | Dosage (mg) | Frequency
Normal | > 80 | 1000 to 3000 | Every 24 h
Mild | 50 to 80 | 1000 to 2000 | Every 24 h
Moderate | 30 to 50 | 500 to 1500 | Every 24 h
Severe | < 30 | 500 to 1000 | Every 24 h

3 DOSAGE FORMS AND STRENGTHS

Levetiracetam extended-release tablets are white, oval-shaped, film-coated extended-release tablets imprinted with “TV/7795” with black ink on one side and plain on the other and contain 500 mg levetiracetam.

Levetiracetam extended-release tablets are white, oval-shaped, film-coated extended-release tablets imprinted with “TV/7796” with black ink on one side and plain on the other and contain 750 mg levetiracetam.

4 CONTRAINDICATIONS

None

5 WARNINGS AND PRECAUTIONS

5.1 Suicidal Behavior and Ideation

Antiepileptic drugs (AEDs), including levetiracetam extended-release tablets, increase the risk of suicidal thoughts or behavior in patients taking these drugs for any indication. Patients treated with any AED for any indication should be monitored for the emergence or worsening of depression, suicidal thoughts or behavior, and/or any unusual changes in mood or behavior.

Pooled analyses of 199 placebo-controlled clinical trials (mono- and adjunctive therapy) of 11 different AEDs showed that patients randomized to one of the AEDs had approximately twice the risk (adjusted Relative Risk 1.8, 95% CI:1.2, 2.7) of suicidal thinking or behavior compared to patients randomized to placebo. In these trials, which had a median treatment duration of 12 weeks, the estimated incidence rate of suicidal behavior or ideation among 27,863 AED-treated patients was 0.43%, compared to 0.24% among 16,029 placebo-treated patients, representing an increase of approximately one case of suicidal thinking or behavior for every 530 patients treated. There were four suicides in drug-treated patients in the trials and none in placebo-treated patients, but the number is too small to allow any conclusion about drug effect on suicide.

The increased risk of suicidal thoughts or behavior with AEDs was observed as early as one week after starting drug treatment with AEDs and persisted for the duration of treatment assessed. Because most trials included in the analysis did not extend beyond 24 weeks, the risk of suicidal thoughts or behavior beyond 24 weeks could not be assessed.

The risk of suicidal thoughts or behavior was generally consistent among drugs in the data analyzed. The finding of increased risk with AEDs of varying mechanisms of action and across a range of indications suggests that the risk applies to all AEDs used for any indication. The risk did not vary substantially by age (5 to 100 years) in the clinical trials analyzed. Table 2 shows absolute and relative risk by indication for all evaluated AEDs.

Table 2 Risk by Indication for Antiepileptic Drugs in the Pooled Analysis
Indication | Placebo Patients with Events Per 1000 Patients | Drug Patients with Events Per 1000 Patients | Relative Risk: Incidence of Events in Drug Patients/Incidence in Placebo Patients | Risk Difference: Additional Drug Patients with Events Per 1000 Patients
Epilepsy | 1.0 | 3.4 | 3.5 | 2.4
Psychiatric | 5.7 | 8.5 | 1.5 | 2.9
Other | 1.0 | 1.8 | 1.9 | 0.9
Total | 2.4 | 4.3 | 1.8 | 1.9

The relative risk for suicidal thoughts or behavior was higher in clinical trials for epilepsy than in clinical trials for psychiatric or other conditions, but the absolute risk differences were similar for the epilepsy and psychiatric indications.

Anyone considering prescribing levetiracetam extended-release tablets or any other AED must balance the risk of suicidal thoughts or behavior with the risk of untreated illness. Epilepsy and many other illnesses for which AEDs are prescribed are themselves associated with morbidity and mortality and an increased risk of suicidal thoughts and behavior. Should suicidal thoughts and behavior emerge during treatment, the prescriber needs to consider whether the emergence of these symptoms in any given patient may be related to the illness being treated.

Patients, their caregivers, and families should be informed that AEDs increase the risk of suicidal thoughts and behavior and should be advised of the need to be alert for the emergence or worsening of the signs and symptoms of depression, any unusual changes in mood or behavior, or the emergence of suicidal thoughts, behavior, or thoughts about self-harm. Behaviors of concern should be reported immediately to healthcare providers.

5.2 Neuropsychiatric Adverse Reactions

Levetiracetam Extended-Release Tablets

In some patients experiencing partial onset seizures, levetiracetam extended-release tablets cause somnolence, dizziness, and behavioral abnormalities.

In the levetiracetam extended-release tablet double-blind, controlled trial in patients experiencing partial onset seizures, 7.8% of levetiracetam extended-release tablet-treated patients experienced somnolence compared to 2.5% of placebo-treated patients. Dizziness was reported in 5.2% of levetiracetam extended-release tablet-treated patients compared to 2.5% of placebo-treated patients.

A total of 6.5% of levetiracetam extended-release tablet-treated patients experienced non-psychotic behavioral disorders (reported as irritability and aggression) compared to 0% of placebo-treated patients. Irritability was reported in 6.5% of levetiracetam extended-release tablet-treated patients. Aggression was reported in 1.3% of levetiracetam extended-release tablet-treated patients.

No patient discontinued treatment or had a dose reduction as a result of these adverse reactions.

The number of patients exposed to levetiracetam extended-release tablets was considerably smaller than the number of patients exposed to immediate-release levetiracetam tablets in controlled trials. Therefore, certain adverse reactions observed in the immediate-release levetiracetam tablet controlled trials may also occur in patients receiving levetiracetam extended-release tablets.

Immediate-Release Levetiracetam Tablets

In controlled trials of immediate-release levetiracetam tablets in patients experiencing partial onset seizures, immediate-release levetiracetam tablets cause the occurrence of central nervous system adverse reactions that can be classified into the following categories: 1) somnolence and fatigue, 2) coordination difficulties, and 3) behavioral abnormalities.

In controlled trials of adult patients with epilepsy experiencing partial onset seizures, 14.8% of immediate-release levetiracetam tablet-treated patients reported somnolence, compared to 8.4% of placebo patients. There was no clear dose response up to 3000 mg/day.

In controlled trials of adult patients with epilepsy experiencing partial onset seizures, 14.7% of treated patients reported asthenia, compared to 9.1% of placebo patients.

A total of 3.4% of immediate-release levetiracetam tablet-treated patients experienced coordination difficulties, (reported as either ataxia, abnormal gait, or incoordination) compared to 1.6% of placebo patients.

Somnolence, asthenia and coordination difficulties occurred most frequently within the first 4 weeks of treatment.

In controlled trials of patients with epilepsy experiencing partial onset seizures, 5 (0.7%) immediate-release levetiracetam tablet-treated patients experienced psychotic symptoms compared to 1 (0.2%) placebo patient.

A total of 13.3% of immediate-release levetiracetam tablet patients experienced other behavioral symptoms (reported as aggression, agitation, anger, anxiety, apathy, depersonalization, depression, emotional lability, hostility, irritability, etc.) compared to 6.2% of placebo patients.

5.3 Withdrawal Seizures

Antiepileptic drugs, including levetiracetam extended-release tablets, should be withdrawn gradually to minimize the potential of increased seizure frequency.

5.4 Hematologic Abnormalities

Although there were no obvious hematologic abnormalities observed in treated patients in the levetiracetam extended-release tablet controlled study, the limited number of patients makes any conclusion tentative. The data from the partial seizure patients in the immediate-release levetiracetam tablet controlled studies should be considered to be relevant for levetiracetam extended-release tablet-treated patients.

In controlled trials of immediate-release levetiracetam tablets in patients experiencing partial onset seizures, minor, but statistically significant, decreases compared to placebo in total mean RBC count (0.03 x 10^6/mm^3), mean hemoglobin (0.09 g/dL), and mean hematocrit (0.38%), were seen in immediate-release levetiracetam tablet-treated patients. A total of 3.2% of treated and 1.8% of placebo patients had at least one possibly significant (≤ 2.8 x 10^9/L) decreased WBC, and 2.4% of treated and 1.4% of placebo patients had at least one possibly significant (≤ 1.0 x 10^9/L) decreased neutrophil count. Of the treated patients with a low neutrophil count, all but one rose towards or to baseline with continued treatment. No patient was discontinued secondary to low neutrophil counts.

5.5 Hepatic Abnormalities

There were no meaningful changes in mean liver function tests (LFT) in the levetiracetam extended-release tablet controlled trial. No patients were discontinued from the controlled trial for LFT abnormalities.

There were no meaningful changes in mean liver function tests (LFT) in controlled trials of immediate-release levetiracetam tablets in adult patients; lesser LFT abnormalities were similar in drug and placebo-treated patients in controlled trials (1.4%). No patients were discontinued from controlled trials for LFT abnormalities except for 1 (0.07%) adult epilepsy patient receiving open treatment.

5.6 Laboratory Tests

Although effects on laboratory tests were not clinically significant with levetiracetam extended-release tablet treatment, it is expected that the data from immediate-release levetiracetam tablets controlled studies would be considered relevant for levetiracetam extended-release tablet-treated patients.

Although most laboratory tests are not systematically altered with immediate-release levetiracetam tablet treatment, there have been relatively infrequent abnormalities seen in hematologic parameters and liver function tests.

6 ADVERSE REACTIONS

6.1 Clinical Studies Experience

Because clinical trials are conducted under widely varying conditions, adverse reaction rates observed in the clinical trials of a drug cannot be directly compared to rates in the clinical trials of another drug and may not reflect the rates observed in practice.

The prescriber should be aware that the adverse reaction incidence figures in the following table, obtained when levetiracetam extended-release tablets were added to concurrent AED therapy, cannot be used to predict the frequency of adverse experiences in the course of usual medical practice where patient characteristics and other factors may differ from those prevailing during clinical studies. Similarly, the cited frequencies cannot be directly compared with figures obtained from other clinical investigations involving different treatments, uses, or investigators. An inspection of these frequencies, however, does provide the prescriber with one basis to estimate the relative contribution of drug and non-drug factors to the adverse reaction incidences in the population studied.

Levetiracetam Extended-Release Tablets

In the well-controlled clinical study using levetiracetam extended-release tablets in patients with partial onset seizures, the most frequently reported adverse reactions in patients receiving levetiracetam extended-release tablets in combination with other AEDs, not seen at an equivalent frequency among placebo-treated patients, were irritability and somnolence.

Table 3 lists treatment-emergent adverse reactions that occurred in at least 5% of epilepsy patients treated with levetiracetam extended-release tablets participating in the placebo-controlled study and were numerically more common than in patients treated with placebo. In this study, either levetiracetam extended-release tablets or placebo was added to concurrent AED therapy. Adverse reactions were usually mild to moderate in intensity.

Table 3: Incidence (%) of Treatment-Emergent Adverse Reactions in the Placebo-Controlled, Add-on Study by Body System (Adverse Reactions Occurred in at Least 5% of Levetiracetam Extended-Release Tablet-Treated Patients and Occurred More Frequently Than Placebo-Treated Patients)
Body System/Adverse Reaction | Levetiracetam Extended-Release Tablets (N = 77) % | Placebo (N = 79) %
Gastrointestinal Disorders
Nausea | 5 | 3
Infections and Infestations
Influenza | 8 | 4
Nasopharyngitis | 7 | 5
Nervous System Disorders
Somnolence | 8 | 3
Dizziness | 5 | 3
Psychiatric Disorders
Irritability | 7 | 0

Discontinuation Or Dose Reduction In The Levetiracetam Extended-Release Tablets Well-Controlled Clinical Study

In the well-controlled clinical study using levetiracetam extended-release tablets, 5.2% of patients receiving levetiracetam extended-release tablets and 2.5% receiving placebo discontinued as a result of an adverse event. The adverse reactions that resulted in discontinuation and that occurred more frequently in levetiracetam extended-release tablet-treated patients than in placebo-treated patients were asthenia, epilepsy, mouth ulceration, rash and respiratory failure. Each of these adverse reactions led to discontinuation in a levetiracetam extended-release tablet-treated patient and no placebo-treated patients.

Comparison Of Gender, Age And Race

There are insufficient data for levetiracetam extended-release tablets to support a statement regarding the distribution of adverse experience reports by gender, age and race.

Table 4 lists the adverse reactions seen in the well-controlled studies of immediate-release levetiracetam tablets in adult patients experiencing partial onset seizures. Although the pattern of adverse reactions in the levetiracetam extended-release tablet study seems somewhat different from that seen in partial onset seizure well-controlled studies for immediate-release levetiracetam tablets, this is possibly due to the much smaller number of patients in this study compared to the immediate-release tablet studies. The adverse reactions for levetiracetam extended-release tablets are expected to be similar to those seen with immediate-release levetiracetam tablets.

Immediate-Release Levetiracetam Tablets

In well-controlled clinical studies of immediate-release levetiracetam tablets as adjunctive therapy to other AEDs in adults with partial onset seizures, the most frequently reported adverse reactions, not seen at an equivalent frequency among placebo-treated patients, were somnolence, asthenia, infection and dizziness.

Table 4 lists treatment-emergent adverse reactions that occurred in at least 1% of adult epilepsy patients treated with immediate-release levetiracetam tablets participating in placebo-controlled studies and were numerically more common than in patients treated with placebo. In these studies, either immediate-release levetiracetam tablets or placebo was added to concurrent AED therapy. Adverse reactions were usually mild to moderate in intensity.

Table 4: Incidence (%) of Treatment-Emergent Adverse Reactions in Placebo-Controlled, Add-on Studies in Adults Experiencing Partial Onset Seizures by Body System (Adverse Reactions Occurred in at Least 1% of Immediate-Release Levetiracetam Tablet-Treated Patients and Occurred More Frequently Than Placebo-Treated Patients)
Body System/Adverse Reaction | Immediate-Release Levetiracetam Tablets (N = 769) % | Placebo (N = 439) %
Body as a Whole
Asthenia | 15 | 9
Headache | 14 | 13
Infection | 13 | 8
Pain | 7 | 6
Digestive System
Anorexia | 3 | 2
Nervous System
Somnolence | 15 | 8
Dizziness | 9 | 4
Depression | 4 | 2
Nervousness | 4 | 2
Ataxia | 3 | 1
Vertigo | 3 | 1
Amnesia | 2 | 1
Anxiety | 2 | 1
Hostility | 2 | 1
Paresthesia | 2 | 1
Emotional Lability | 2 | 0
Respiratory System
Pharyngitis | 6 | 4
Rhinitis | 4 | 3
Cough Increased | 2 | 1
Sinusitis | 2 | 1
Special Senses
Diplopia | 2 | 1

In addition, the following adverse reactions were seen in other well-controlled studies of immediate-release levetiracetam tablets: balance disorder, disturbance in attention, eczema, hyperkinesia, memory impairment, myalgia, personality disorders, pruritus, and vision blurred.

6.2 Postmarketing Experience

In addition to the adverse reactions listed above for immediate-release levetiracetam tablets [see Adverse Reactions (6.1)], the following adverse events have been identified during postapproval use of immediate-release levetiracetam tablets. Because these events are reported voluntarily from a population of uncertain size, it is not always possible to reliably estimate their frequency or establish a causal relationship to drug exposure. The listing is alphabetized: abnormal liver function test, hepatic failure, hepatitis, leukopenia, neutropenia, pancreatitis, pancytopenia (with bone marrow suppression identified in some of these cases), thrombocytopenia and weight loss. Alopecia has been reported with immediate-release levetiracetam tablet use; recovery was observed in majority of cases where immediate-release levetiracetam tablets were discontinued.

7 DRUG INTERACTIONS

7.1 General Information

In vitro data on metabolic interactions indicate that levetiracetam extended-release tablets are unlikely to produce, or be subject to, pharmacokinetic interactions. Levetiracetam and its major metabolite, at concentrations well above Cmax levels achieved within the therapeutic dose range, are neither inhibitors of nor high affinity substrates for human liver cytochrome P450 isoforms, epoxide hydrolase or UDP-glucuronidation enzymes. In addition, levetiracetam does not affect the in vitro glucuronidation of valproic acid.

Levetiracetam circulates largely unbound (< 10% bound) to plasma proteins; clinically significant interactions with other drugs through competition for protein binding sites are therefore unlikely.

Potential pharmacokinetic interactions were assessed in clinical pharmacokinetic studies (phenytoin, valproate, oral contraceptive, digoxin, warfarin, probenecid) and through pharmacokinetic screening with immediate-release levetiracetam tablets in the placebo-controlled clinical studies in epilepsy patients. The following are the results of these studies. The potential for drug interactions for levetiracetam extended-release tablets is expected to be essentially the same as that with immediate-release levetiracetam tablets.

7.2 Phenytoin

Immediate-release levetiracetam tablets (3000 mg daily) had no effect on the pharmacokinetic disposition of phenytoin in patients with refractory epilepsy. Pharmacokinetics of levetiracetam were also not affected by phenytoin.

7.3 Valproate

Immediate-release levetiracetam tablets (1500 mg twice daily) did not alter the pharmacokinetics of valproate in healthy volunteers. Valproate 500 mg twice daily did not modify the rate or extent of levetiracetam absorption or its plasma clearance or urinary excretion. There also was no effect on exposure to and the excretion of the primary metabolite, ucb L057.

7.4 Other Antiepileptic Drugs

Potential drug interactions between immediate-release levetiracetam tablets and other AEDs (carbamazepine, gabapentin, lamotrigine, phenobarbital, phenytoin, primidone and valproate) were also assessed by evaluating the serum concentrations of levetiracetam and these AEDs during placebo-controlled clinical studies. These data indicate that levetiracetam does not influence the plasma concentration of other AEDs and that these AEDs do not influence the pharmacokinetics of levetiracetam.

7.5 Oral Contraceptives

Immediate-release levetiracetam tablets (500 mg twice daily) did not influence the pharmacokinetics of an oral contraceptive containing 0.03 mg ethinyl estradiol and 0.15 mg levonorgestrel, or of the luteinizing hormone and progesterone levels, indicating that impairment of contraceptive efficacy is unlikely. Coadministration of this oral contraceptive did not influence the pharmacokinetics of levetiracetam.

7.6 Digoxin

Immediate-release levetiracetam tablets (1000 mg twice daily) did not influence the pharmacokinetics and pharmacodynamics (ECG) of digoxin given as a 0.25 mg dose every day. Coadministration of digoxin did not influence the pharmacokinetics of levetiracetam.

7.7 Warfarin

Immediate-release levetiracetam tablets (1000 mg twice daily) did not influence the pharmacokinetics of R and S warfarin. Prothrombin time was not affected by levetiracetam. Coadministration of warfarin did not affect the pharmacokinetics of levetiracetam.

7.8 Probenecid

Probenecid, a renal tubular secretion blocking agent, administered at a dose of 500 mg four times a day, did not change the pharmacokinetics of levetiracetam 1000 mg twice daily. Cssmax of the metabolite, ucb L057, was approximately doubled in the presence of probenecid while the fraction of drug excreted unchanged in the urine remained the same. Renal clearance of ucb L057 in the presence of probenecid decreased 60%, probably related to competitive inhibition of tubular secretion of ucb L057. The effect of immediate-release levetiracetam tablets on probenecid was not studied.

8 USE IN SPECIFIC POPULATIONS

8.1 Pregnancy

Teratogenic Effects

Pregnancy category C

There are no adequate and well-controlled studies in pregnant women. In animal studies, levetiracetam produced evidence of developmental toxicity, including teratogenic effects, at doses similar to or greater than human therapeutic doses. Levetiracetam extended-release tablets should be used during pregnancy only if the potential benefit justifies the potential risk to the fetus.

Oral administration of levetiracetam to female rats throughout pregnancy and lactation led to increased incidences of minor fetal skeletal abnormalities and retarded offspring growth pre- and/or postnatally at doses ≥ 350 mg/kg/day (approximately equivalent to the maximum recommended human dose of 3000 mg [MRHD] on a mg/m^2 basis) and with increased pup mortality and offspring behavioral alterations at a dose of 1800 mg/kg/day (6 times the MRHD on a mg/m^2 basis). The developmental no effect dose was 70 mg/kg/day (0.2 times the MRHD on a mg/m^2 basis). There was no overt maternal toxicity at the doses used in this study.

Oral administration of levetiracetam to pregnant rabbits during the period of organogenesis resulted in increased embryofetal mortality and increased incidences of minor fetal skeletal abnormalities at doses ≥ 600 mg/kg/day (approximately 4 times MRHD on a mg/m^2 basis) and in decreased fetal weights and increased incidences of fetal malformations at a dose of 1800 mg/kg/day (12 times the MRHD on a mg/m^2 basis). The developmental no effect dose was 200 mg/kg/day (1.3 times the MRHD on a mg/m^2 basis). Maternal toxicity was also observed at 1800 mg/kg/day.

When levetiracetam was administered orally to pregnant rats during the period of organogenesis, fetal weights were decreased and the incidence of fetal skeletal variations was increased at a dose of 3600 mg/kg/day (12 times the MRHD). 1200 mg/kg/day (4 times the MRHD) was a developmental no effect dose. There was no evidence of maternal toxicity in this study.

Treatment of rats with levetiracetam during the last third of gestation and throughout lactation produced no adverse developmental or maternal effects at oral doses of up to 1800 mg/kg/day (6 times the MRHD on a mg/m^2 basis).

Pregnancy Registry

To provide information regarding the effects of in utero exposure to levetiracetam extended-release tablets, physicians are advised to recommend that pregnant patients taking levetiracetam extended-release tablets enroll in the North American Antiepileptic Drug (NAAED) pregnancy registry. This can be done by calling the toll free number 1-888-233-2334, and must be done by the patients themselves. Information on the registry can also be found at the website http://www.aedpregnancyregistry.org/.

8.2 Labor and Delivery

The effect of levetiracetam extended-release tablets on labor and delivery in humans is unknown.

8.3 Nursing Mothers

Levetiracetam is excreted in breast milk. Because of the potential for serious adverse reactions in nursing infants from levetiracetam extended-release tablets, a decision should be made whether to discontinue nursing or discontinue the drug, taking into account the importance of the drug to the mother.

8.4 Pediatric Use

Safety and effectiveness of levetiracetam extended-release tablets in patients below the age of 16 years have not been established.

8.5 Geriatric Use

There were insufficient numbers of elderly subjects in controlled trials of epilepsy to adequately assess the effectiveness of levetiracetam extended-release tablets in these patients. It is expected that the safety of levetiracetam extended-release tablets in elderly patients 65 and over would be comparable to the safety observed in clinical studies of immediate-release levetiracetam tablets.

Of the total number of subjects in clinical studies of immediate-release levetiracetam tablets, 347 were 65 and over. No overall differences in safety were observed between these subjects and younger subjects. There were insufficient numbers of elderly subjects in controlled trials of epilepsy to adequately assess the effectiveness of immediate-release levetiracetam tablets in these patients.

A study in 16 elderly subjects (age 61 to 88 years) with oral administration of single dose and multiple twice-daily doses of immediate-release levetiracetam tablets for 10 days showed no pharmacokinetic differences related to age alone.

Levetiracetam is known to be substantially excreted by the kidney, and the risk of adverse reactions to this drug may be greater in patients with impaired renal function. Because elderly patients are more likely to have decreased renal function, care should be taken in dose selection, and it may be useful to monitor renal function.

8.6 Use in Patients With Impaired Renal Function

The effect of levetiracetam extended-release tablets on renally impaired patients was not assessed in the well-controlled study. However, it is expected that the effect on levetiracetam extended-release tablet-treated patients would be similar to the effect seen in well-controlled studies of immediate-release levetiracetam tablets. Caution should be taken in dosing patients with moderate and severe renal impairment and in patients undergoing hemodialysis. The dosage should be reduced in patients with impaired renal function receiving levetiracetam extended-release tablets [see Clinical Pharmacology (12.3) and Dosage and Administration (2.1)].

Clearance of immediate-release levetiracetam tablets is decreased in patients with renal impairment and is correlated with creatinine clearance.

9 DRUG ABUSE AND DEPENDENCE

The abuse and dependence potential of levetiracetam extended-release tablets has not been evaluated in human studies.

10 OVERDOSAGE

Signs, Symptoms And Laboratory Findings Of Acute Overdosage In Humans

The signs and symptoms for levetiracetam extended-release tablet overdose are expected to be similar to those seen with immediate-release levetiracetam tablets.

The highest known dose of oral immediate-release levetiracetam received in the clinical development program was 6000 mg/day. Other than drowsiness, there were no adverse reactions in the few known cases of overdose in clinical trials. Cases of somnolence, agitation, aggression, depressed level of consciousness, respiratory depression and coma were observed with immediate-release levetiracetam tablet overdoses in postmarketing use.

Treatment Or Management Of Overdose

There is no specific antidote for overdose with levetiracetam extended-release tablets. If indicated, elimination of unabsorbed drug should be attempted by emesis or gastric lavage; usual precautions should be observed to maintain airway. General supportive care of the patient is indicated including monitoring of vital signs and observation of the patient’s clinical status. A Certified Poison Control Center should be contacted for up to date information on the management of overdose with levetiracetam extended-release tablets.

Hemodialysis

Standard hemodialysis procedures result in significant clearance of levetiracetam (approximately 50% in 4 hours) and should be considered in cases of overdose. Although hemodialysis has not been performed in the few known cases of overdose, it may be indicated by the patient's clinical state or in patients with significant renal impairment.

11 DESCRIPTION

Levetiracetam extended-release tablets are an antiepileptic drug available as 500 mg and 750 mg (white) extended-release tablets for oral administration.

The chemical name of levetiracetam, a single enantiomer, is (-)-(S)-α-ethyl-2-oxo-1-pyrrolidine acetamide. Levetiracetam is chemically unrelated to existing antiepileptic drugs (AEDs). It has the following structural formula:

C8H14N2O2 M.W. 170.21

Levetiracetam is a white to off-white crystalline powder with a faint odor and a bitter taste. It is very soluble in water (104.0 g/100 mL). It is freely soluble in chloroform (65.3 g/100 mL) and in methanol (53.6 g/100 mL), soluble in ethanol (16.5 g/100 mL), sparingly soluble in acetonitrile (5.7 g/100 mL) and practically insoluble in n-hexane. (Solubility limits are expressed as g/100 mL solvent.)

Levetiracetam extended-release tablets contain the labeled amount of levetiracetam. Inactive ingredients: dibutyl sebacate, ethylcellulose, hydrogenated castor oil powder, hypromellose, magnesium stearate, microcrystalline cellulose, polyethylene glycol, povidone, and titanium dioxide. The imprinting ink contains iron oxide black and shellac glaze.

12 CLINICAL PHARMACOLOGY

12.1 Mechanism of Action

The precise mechanism(s) by which levetiracetam exerts its antiepileptic effect is unknown. The antiepileptic activity of levetiracetam was assessed in a number of animal models of epileptic seizures. Levetiracetam did not inhibit single seizures induced by maximal stimulation with electrical current or different chemoconvulsants and showed only minimal activity in submaximal stimulation and in threshold tests. Protection was observed, however, against secondarily generalized activity from focal seizures induced by pilocarpine and kainic acid, two chemoconvulsants that induce seizures that mimic some features of human complex partial seizures with secondary generalization. Levetiracetam also displayed inhibitory properties in the kindling model in rats, another model of human complex partial seizures, both during kindling development and in the fully kindled state. The predictive value of these animal models for specific types of human epilepsy is uncertain.

In vitro and in vivo recordings of epileptiform activity from the hippocampus have shown that levetiracetam inhibits burst firing without affecting normal neuronal excitability, suggesting that levetiracetam may selectively prevent hypersynchronization of epileptiform burst firing and propagation of seizure activity.

Levetiracetam at concentrations of up to 10 μM did not demonstrate binding affinity for a variety of known receptors, such as those associated with benzodiazepines, GABA (gamma-aminobutyric acid), glycine, NMDA (N-methyl-D-aspartate), re-uptake sites, and second messenger systems. Furthermore, in vitro studies have failed to find an effect of levetiracetam on neuronal voltage-gated sodium or T-type calcium currents and levetiracetam does not appear to directly facilitate GABAergic neurotransmission. However, in vitro studies have demonstrated that levetiracetam opposes the activity of negative modulators of GABA- and glycine-gated currents and partially inhibits N-type calcium currents in neuronal cells.

A saturable and stereoselective neuronal binding site in rat brain tissue has been described for levetiracetam. Experimental data indicate that this binding site is the synaptic vesicle protein SV2A, thought to be involved in the regulation of vesicle exocytosis. Although the molecular significance of levetiracetam binding to synaptic vesicle protein SV2A is not understood, levetiracetam and related analogs showed a rank order of affinity for SV2A which correlated with the potency of their antiseizure activity in audiogenic seizure-prone mice. These findings suggest that the interaction of levetiracetam with the SV2A protein may contribute to the antiepileptic mechanism of action of the drug.

12.3 Pharmacokinetics

Overview

Bioavailability of levetiracetam extended-release tablets is similar to that of the levetiracetam immediate-release tablets. The pharmacokinetics (AUC and Cmax) were shown to be dose proportional after single dose administration of 1000 mg, 2000 mg, and 3000 mg extended-release levetiracetam. Plasma half-life of extended-release levetiracetam is approximately 7 hours.

Levetiracetam is almost completely absorbed after oral administration. The pharmacokinetics of levetiracetam are linear and time-invariant, with low intra- and inter-subject variability. Levetiracetam is not significantly protein-bound (< 10% bound) and its volume of distribution is close to the volume of intracellular and extracellular water. Sixty-six percent (66%) of the dose is renally excreted unchanged. The major metabolic pathway of levetiracetam (24% of dose) is an enzymatic hydrolysis of the acetamide group. It is not liver cytochrome P450 dependent. The metabolites have no known pharmacological activity and are renally excreted. Plasma half-life of levetiracetam across studies is approximately 6 to 8 hours. The half-life is increased in the elderly (primarily due to impaired renal clearance) and in subjects with renal impairment.

Absorption and Distribution

Extended-release levetiracetam peak plasma concentrations occur in about 4 hours. The time to peak plasma concentrations is about 3 hours longer with extended-release levetiracetam than with immediate-release tablets.

Single administration of two 500 mg extended-release levetiracetam tablets once daily produced comparable maximal plasma concentrations and area under the plasma concentration versus time as did the administration of one 500 mg immediate-release tablet twice daily in fasting conditions. After multiple dose extended-release levetiracetam tablets intake, extent of exposure (AUC0-24) was similar to extent of exposure after multiple dose immediate-release tablets intake. Cmax and Cmin were lower by 17% and 26% after multiple dose extended-release levetiracetam tablets intake in comparison to multiple dose immediate-release tablets intake. Intake of a high fat, high calorie breakfast before the administration of extended-release levetiracetam tablets resulted in a higher peak concentration, and longer median time to peak. The median time to peak (Tmax) was 2 hours longer in the fed state.

Two 750 mg extended-release levetiracetam tablets were bioequivalent to a single administration of three 500 mg extended-release levetiracetam tablets.

Metabolism

Levetiracetam is not extensively metabolized in humans. The major metabolic pathway is the enzymatic hydrolysis of the acetamide group, which produces the carboxylic acid metabolite, ucb L057 (24% of dose) and is not dependent on any liver cytochrome P450 isoenzymes. The major metabolite is inactive in animal seizure models. Two minor metabolites were identified as the product of hydroxylation of the 2-oxo-pyrrolidine ring (2% of dose) and opening of the 2-oxo-pyrrolidine ring in position 5 (1% of dose). There is no enantiomeric interconversion of levetiracetam or its major metabolite.

Elimination

Levetiracetam plasma half-life in adults is 7 ± 1 hour and is unaffected by either dose or repeated administration. Levetiracetam is eliminated from the systemic circulation by renal excretion as unchanged drug which represents 66% of administered dose. The total body clearance is 0.96 mL/min/kg and the renal clearance is 0.6 mL/min/kg. The mechanism of excretion is glomerular filtration with subsequent partial tubular reabsorption. The metabolite ucb L057 is excreted by glomerular filtration and active tubular secretion with a renal clearance of 4 mL/min/kg. Levetiracetam elimination is correlated to creatinine clearance. Levetiracetam clearance is reduced in patients with impaired renal function [see Use in Specific Populations (8.6) and Dosage and Administration (2.1)].

Pharmacokinetic Interactions

In vitro data on metabolic interactions indicate that levetiracetam is unlikely to produce, or be subject to, pharmacokinetic interactions. Levetiracetam and its major metabolite, at concentrations well above Cmax levels achieved within the therapeutic dose range, are neither inhibitors of, nor high affinity substrates for, human liver cytochrome P450 isoforms, epoxide hydrolase or UDP-glucuronidation enzymes. In addition, levetiracetam does not affect the in vitro glucuronidation of valproic acid. The pharmacokinetics of immediate-release levetiracetam are linear over the dose range of 500 to 5000 mg. Levetiracetam and its major metabolite are less than 10% bound to plasma proteins; clinically significant interactions with other drugs through competition for protein binding sites are therefore unlikely.

Potential pharmacokinetic interactions of or with immediate-release levetiracetam were assessed in clinical pharmacokinetic studies (phenytoin, valproate, warfarin, digoxin, oral contraceptive, probenecid) and through pharmacokinetic screening in the placebo-controlled clinical studies in epilepsy patients [see Drug Interactions (7)]. The potential for drug interactions for extended-release levetiracetam is expected to be similar to that with immediate-release levetiracetam.

Special Populations

Elderly

There are insufficient pharmacokinetic data to specifically address the use of extended-release levetiracetam in the elderly population.

Pharmacokinetics of immediate-release levetiracetam were evaluated in 16 elderly subjects (age 61 to 88 years) with creatinine clearance ranging from 30 to 74 mL/min. Following oral administration of twice-daily dosing for 10 days, total body clearance decreased by 38% and the half-life was 2.5 hours longer in the elderly compared to healthy adults. This is most likely due to the decrease in renal function in these subjects.

Pediatric Patients

Safety and effectiveness of levetiracetam extended-release tablets in patients below the age of 16 years have not been established.

Gender

Extended-release levetiracetam Cmax was 21 to 30% higher and AUC was 8 to 18% higher in women (N = 12) compared to men (N = 12). However, clearances adjusted for body weight were comparable.

Race

Formal pharmacokinetic studies of the effects of race have not been conducted with extended-release or immediate-release levetiracetam. Cross study comparisons involving Caucasians (N = 12) and Asians (N = 12), however, show that pharmacokinetics of immediate-release levetiracetam were comparable between the two races.

Renal Impairment

The effect of levetiracetam extended-release tablets on renally impaired patients was not assessed in the well-controlled study. However, it is expected that the effect on levetiracetam extended-release-treated patients would be similar to that seen in well-controlled studies of immediate-release levetiracetam tablets. In patients with end stage renal disease on dialysis, it is recommended that immediate-release levetiracetam be used instead of levetiracetam extended-release tablets.

The disposition of immediate-release levetiracetam was studied in adult subjects with varying degrees of renal function. Total body clearance of levetiracetam is reduced in patients with impaired renal function by 40% in the mild group (CLcr = 50 to 80 mL/min), 50% in the moderate group (CLcr = 30 to 50 mL/min) and 60% in the severe renal impairment group (CLcr < 30 mL/min). Clearance of levetiracetam is correlated with creatinine clearance.

In anuric (end stage renal disease) patients, the total body clearance decreased 70% compared to normal subjects (CLcr > 80 mL/min). Approximately 50% of the pool of levetiracetam in the body is removed during a standard 4 hour hemodialysis procedure.

Dosage should be reduced in patients with impaired renal function receiving levetiracetam; immediate-release levetiracetam should be given to patients on dialysis [see Dosage and Administration (2.1)].

Hepatic Impairment

In subjects with mild (Child-Pugh A) to moderate (Child-Pugh B) hepatic impairment, the pharmacokinetics of levetiracetam were unchanged. In patients with severe hepatic impairment (Child-Pugh C), total body clearance was 50% that of normal subjects, but decreased renal clearance accounted for most of the decrease. No dose adjustment is needed for patients with hepatic impairment.

13 NONCLINICAL TOXICOLOGY

13.1 Carcinogenesis, Mutagenesis, Impairment of Fertility

Carcinogenesis

Rats were dosed with levetiracetam in the diet for 104 weeks at doses of 50, 300 and 1800 mg/kg/day. The highest dose corresponds to 6 times the maximum recommended daily human dose (MRHD) of 3000 mg on a mg/m^2 basis and it also provided systemic exposure (AUC) approximately 6 times that achieved in humans receiving the MRHD. There was no evidence of carcinogenicity. A study was conducted in which mice received levetiracetam in the diet for 80 weeks at doses of 60, 240 and 960 mg/kg/day (high dose is equivalent to 2 times the MRHD on a mg/m^2 or exposure basis). Although no evidence for carcinogenicity was seen, the potential for a carcinogenic response has not been fully evaluated in that species because adequate doses have not been studied.

Mutagenesis

Levetiracetam was not mutagenic in the Ames test or in mammalian cells in vitro in the Chinese hamster ovary/HGPRT locus assay. It was not clastogenic in an in vitro analysis of metaphase chromosomes obtained from Chinese hamster ovary cells or in an in vivo mouse micronucleus assay. The hydrolysis product and major human metabolite of levetiracetam (ucb L057) was not mutagenic in the Ames test or the in vitro mouse lymphoma assay.

Impairment Of Fertility

No adverse effects on male or female fertility or reproductive performance were observed in rats at oral doses up to 1800 mg/kg/day (approximately 6 times the maximum recommended human dose on a mg/m^2 or exposure basis).

13.2 Animal Toxicology and/or Pharmacology

In animal studies, levetiracetam produced evidence of developmental toxicity at doses similar to or greater than human therapeutic doses.

14 CLINICAL STUDIES

The effectiveness of the immediate-release formulation of levetiracetam as adjunctive therapy (added to other antiepileptic drugs) in adults was established in three multicenter, randomized, double-blind, placebo controlled clinical studies in 904 patients who had refractory partial onset seizures with or without secondary generalization for at least two years and had taken two or more classical AEDs.

The effectiveness of levetiracetam extended-release tablets as adjunctive therapy (added to other antiepileptic drugs) was established in one multicenter, randomized, double-blind, placebo-controlled clinical study across 7 countries in patients who had refractory partial onset seizures with or without secondary generalization. Patients enrolled had at least eight partial seizures with or without secondary generalization during the 8 week baseline period and at least two partial seizures in each 4 week interval of the baseline period. Patients were taking a stable dose regimen of at least one and could take a maximum of three AEDs. After a prospective baseline period of 8 weeks, 158 patients were randomized to placebo (N = 79) or levetiracetam extended-release tablets (2 x 500 mg tablets) (N = 79) given once daily over a 12 week treatment period.

The primary efficacy endpoint was the percent reduction over placebo in mean weekly frequency of partial onset seizures. The median percent reduction in weekly partial onset seizure frequency from baseline over the treatment period was 46.1% in the levetiracetam extended-release tablet 1000 mg treatment group (N = 74) and 33.4% in the placebo group (N = 78). The estimated percent reduction over placebo in weekly partial onset seizure frequency over the treatment period was 14.4% (statistically significant).

The relationship between the effectiveness of the same daily dose of levetiracetam extended-release tablets and immediate-release levetiracetam has not been studied and is unknown.

16 HOW SUPPLIED/STORAGE AND HANDLING

16.1 How Supplied

Levetiracetam extended-release tablets are available as follows:

500 mg – white, oval-shaped, film-coated tablets imprinted with “TV/7795” with black ink on one side and plain on the other, in bottles of 90.....NDC 54868-6316-0.

16.2 Storage

Store at 20° to 25°C (68° to 77°F) [See USP Controlled Room Temperature].

Dispense in a tight, light-resistant container as defined in the USP, with a child-resistant closure (as required).

17 PATIENT COUNSELING INFORMATION

Patients and caregivers should be informed of the availability of a Medication Guide, and they should be instructed to read the Medication Guide prior to taking levetiracetam extended-release tablets. The Medication Guide may also obtained by calling 1-888-838-2872, MEDICAL AFFAIRS. Patients should be instructed to take levetiracetam extended-release tablets only as prescribed.

Patients, their caregivers, and families should be counseled that AEDs, including levetiracetam extended-release tablets, may increase the risk of suicidal thoughts and behavior and should be advised of the need to be alert for the emergence or worsening of symptoms of depression, any unusual changes in mood or behavior, or the emergence of suicidal thoughts, behavior, or thoughts about self-harm. Behaviors of concern should be reported immediately to healthcare providers.

Patients should be advised that levetiracetam extended-release tablets may cause irritability and aggression. In addition, patients should be advised that they may experience changes in behavior that have been seen with other formulations of levetiracetam, which include agitation, anger, anxiety, apathy, depression, hostility, irritability and, in rare cases, psychotic symptoms.

Patients should be instructed to only take levetiracetam extended-release tablets as prescribed and to swallow the tablets whole. They should not be chewed, broken, or crushed.

Patients should be advised to notify their physician if they become pregnant or intend to become pregnant during therapy. Patients should be encouraged to enroll in the NAAED Pregnancy Registry if they become pregnant. This registry is collecting information about the safety of antiepileptic drugs during pregnancy. To enroll, patients can call the toll free number 1-888-233-2334 [see Use in Specific Populations (8.1)].

Patients should be advised that levetiracetam extended-release tablets may cause dizziness and somnolence. Accordingly, patients should be advised not to drive or operate heavy machinery or engage in other hazardous activities until they have gained sufficient experience on levetiracetam extended-release tablets to gauge whether they adversely affect their performance of these activities.

Manufactured In Israel By:

TEVA PHARMACEUTICAL IND. LTD.

Jerusalem, 91010, Israel

Manufactured For:

TEVA PHARMACEUTICALS USA

Sellersville, PA 18960

Rev. A 1/2011

Relabeling and Repackaging by:
Physicians Total Care, Inc.
Tulsa, Oklahoma 74146

MEDICATION GUIDE

Levetiracetam Extended-Release Tablets

Read this Medication Guide before you start taking levetiracetam extended-release tablets and each time you get a refill. There may be new information. This information does not take the place of talking to your healthcare provider about your medical condition or treatment.

What is the most important information I should know about levetiracetam extended-release tablets?

Like other antiepileptic drugs, levetiracetam extended-release tablets may cause suicidal thoughts or actions in a very small number of people, about 1 in 500 people taking them.

Call a healthcare provider right away if you have any of these symptoms, especially if they are new, worse, or worry you:

- thoughts about suicide or dying
- attempts to commit suicide
- new or worse depression
- new or worse anxiety
- feeling agitated or restless
- panic attacks
- trouble sleeping (insomnia)
- new or worse irritability
- acting aggressive, being angry, or violent
- acting on dangerous impulses
- an extreme increase in activity and talking (mania)
- other unusual changes in behavior or mood

Do not stop levetiracetam extended-release tablets without first talking to a healthcare provider.

- Stopping levetiracetam extended-release tablets suddenly can cause serious problems. Stopping a seizure medicine suddenly can cause seizures that will not stop (status epilepticus).
- Suicidal thoughts or actions can be caused by things other than medicines. If you have suicidal thoughts or actions, your healthcare provider may check for other causes.

How can I watch for early symptoms of suicidal thoughts and actions?

- Pay attention to any changes, especially sudden changes, in mood, behaviors, thoughts, or feelings.
- Keep all follow-up visits with your healthcare provider as scheduled.
- Call your healthcare provider between visits as needed, especially if you are worried about symptoms.

What are levetiracetam extended-release tablets?

Levetiracetam extended-release tablets are a prescription medicine taken by mouth that is used with other medicines to treat partial onset seizures in people 16 years of age and older with epilepsy.

It is not known if levetiracetam extended-release tablets are safe or effective in people under 16 years of age.

Before taking your medicine, make sure you have received the correct medicine. Compare the name above with the name on your bottle and the appearance of your medicine with the description of levetiracetam extended-release tablets provided below. Tell your pharmacist immediately if you think you have been given the wrong medicine.

500 mg levetiracetam extended-release tablets are white, oval-shaped, film-coated extended-release tablets imprinted with “TV/7795” with black ink on one side and plain on the other.

750 mg levetiracetam extended-release tablets are white, oval-shaped, film-coated extended-release tablets imprinted with “TV/7796” with black ink on one side and plain on the other.

What should I tell my healthcare provider before starting levetiracetam extended-release tablets?

Before taking levetiracetam extended-release tablets, tell your healthcare provider about all of your medical conditions, including if you:

- have or have had depression, mood problems or suicidal thoughts or behavior
- have kidney problems
- are pregnant or planning to become pregnant. It is not known if levetiracetam extended-release tablets will harm your unborn baby. You and your healthcare provider will have to decide if you should take levetiracetam extended-release tablets while you are pregnant. If you become pregnant while taking levetiracetam extended-release tablets, talk to your healthcare provider about registering with the North American Antiepileptic Drug Pregnancy Registry. You can enroll in this registry by calling 1-888-233-2334. The purpose of this registry is to collect information about the safety of levetiracetam extended-release tablets and other antiepileptic medicine during pregnancy.
- are breast feeding. Levetiracetam can pass into your milk and may harm your baby. You and your healthcare provider should discuss whether you should take levetiracetam extended-release tablets or breast feed; you should not do both.

Tell your healthcare provider about all the medicines you take, including prescription and nonprescription medicines, vitamins, and herbal supplements. Do not start a new medicine without first talking with your healthcare provider.

Know the medicines you take. Keep a list of them to show your healthcare provider and pharmacist each time you get a new medicine.

How should I take levetiracetam extended-release tablets?

Take levetiracetam extended-release tablets exactly as prescribed.

- Your healthcare provider will tell you how many levetiracetam extended-release tablets to take and when to take them. Levetiracetam extended-release tablets are usually taken once a day. Take levetiracetam extended-release tablets at the same time each day.
- Your healthcare provider may change your dose. Do not change your dose without talking to your healthcare provider.
- Take levetiracetam extended-release tablets with or without food.
- Swallow the tablets whole. Do not chew, break, or crush tablets.
- If you miss a dose of levetiracetam extended-release tablets, take it as soon as you remember. If it is almost time for your next dose, just skip the missed dose. Take the next dose at your regular time. Do not take two doses at the same time.
- If you take too many levetiracetam extended-release tablets, call your local Poison Control Center or go to the nearest emergency room right away.

What should I avoid while taking levetiracetam extended-release tablets?

Do not drive, operate machinery or do other dangerous activities until you know how levetiracetam extended-release tablets affect you. Levetiracetam extended-release tablets may make you dizzy or sleepy.

What are the possible side effects of levetiracetam extended-release tablets?

- See “What is the most important information I should know aboutlevetiracetam extended-release tablets?”

Levetiracetam extended-release tablets can cause serious side effects.

Call your healthcare provider right away if you have any of these symptoms:

- mood and behavior changes such as aggression, agitation, anger, anxiety, apathy, mood swings, depression, hostility, and irritability. A few people may get psychotic symptoms such as hallucinations (seeing or hearing things that are really not there), delusions (false or strange thoughts or beliefs) and unusual behavior.
- extreme sleepiness, tiredness, and weakness
- problems with muscle coordination (problems walking and moving)

Common side effects seen in people who take levetiracetam extended-release tablets and other formulations of levetiracetam include:

- sleepiness
- weakness
- dizziness
- infection

These side effects can happen at any time but happen more often within the first 4 weeks of treatment.

Tell your healthcare provider if you have any side effect that bothers you or that does not go away.

These are not all the possible side effects of levetiracetam extended-release tablets. For more information, ask your healthcare provider or pharmacist.

Call your doctor for medical advice about side effects. You may also report side effects to FDA at 1-800-FDA-1088.

How should I store levetiracetam extended-release tablets?

- Store levetiracetam extended-release tablets at room temperature, 20° to 25°C (68° to 77°F) away from heat and light.
- Keep levetiracetam extended-release tablets and all medicines out of the reach of children.

General information about levetiracetam extended-release tablets.

Medicines are sometimes prescribed for purposes other than those listed in a Medication Guide. Do not use levetiracetam extended-release tablets for a condition for which they were not prescribed. Do not give levetiracetam extended-release tablets to other people, even if they have the same symptoms that you have. They may harm them.

This Medication Guide summarizes the most important information about levetiracetam extended-release tablets. If you would like more information, talk with your healthcare provider. You can ask your pharmacist or healthcare provider for information about levetiracetam extended-release tablets that is written for health professionals. You can also get information about levetiracetam extended-release tablets by calling 1-888-838-2872, MEDICAL AFFAIRS.

What are the ingredients of levetiracetam extended-release tablets?

Levetiracetam extended-release tablet active ingredient: levetiracetam

Inactive ingredients: dibutyl sebacate, ethylcellulose, hydrogenated castor oil powder, hypromellose, magnesium stearate, microcrystalline cellulose, polyethylene glycol, povidone, and titanium dioxide. The imprinting ink contains iron oxide black and shellac glaze.

Levetiracetam extended-release tablets do not contain lactose or gluten.

This Medication Guide has been approved by the US Food and Drug Administration.

Manufactured In Israel By:

TEVA PHARMACEUTICAL IND. LTD.

Jerusalem, 91010, Israel

Manufactured For:

TEVA PHARMACEUTICALS USA

Sellersville, PA 18960

Rev. A 1/2011

PRINCIPAL DISPLAY PANEL

Levetiracetam Extended-Release Tablets 500 mg Label Text

LEVETIRACETAM

Extended-Release

Tablets

500 mg

Once Daily Dosing

PHARMACIST: Dispense the accompanying

Medication Guide to each patient.

Rx only